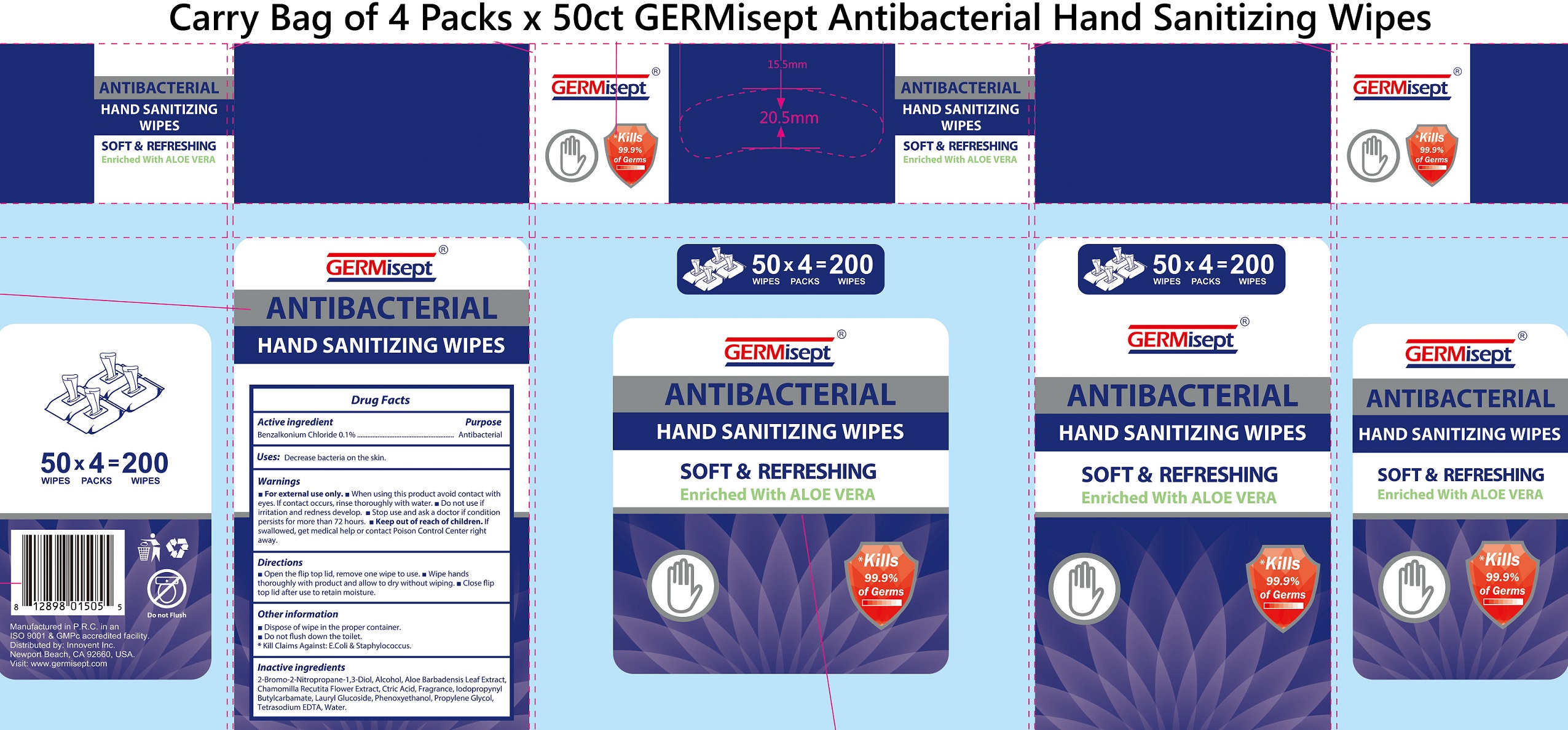 DRUG LABEL: GERMisept Antibacterial Hand Sanitizing Wipes
NDC: 70335-012 | Form: CLOTH
Manufacturer: Innovent Inc
Category: otc | Type: HUMAN OTC DRUG LABEL
Date: 20231221

ACTIVE INGREDIENTS: BENZALKONIUM CHLORIDE 1 mg/1 mL
INACTIVE INGREDIENTS: BRONOPOL; ALCOHOL; ALOE VERA LEAF; CITRIC ACID MONOHYDRATE; IODOPROPYNYL BUTYLCARBAMATE; LAURYL GLUCOSIDE; PHENOXYETHANOL; PROPYLENE GLYCOL; EDETATE SODIUM; WATER

GERMisept Antibacterial Hand Sanitizing Wipes

Active ingredient

Benzalkonium Chloride 0.1%

Purpose

Antibacterial

Uses:

Decrease bacteria on the skin.

Warnings

- For external use only.

When using this product

- avoid contact with eyes. If contact occurs, rinse thoroughly with water.

Do not use

if irritation and redness develop.

Stop use and ask a doctor

if condition persists for more than 72 hours.

Keep out of reach of children.

If swallowed, get medical help or contact Poison Control Center right away.

Directions

- Open the flip top lid, remove one wipe to use.
- Wipe hands thoroughly the product and allow to dry without wiping.
- Close flip top lid after use to retain moisture.

Other information

- Dispose of wipe in the proper container.
- Do not flush down the toilet.

*Kill Claims Against: E.Coli & Staphylococcus.

Inactive ingredients

2-Bromo-2-Nitropropane-1,3-Diol, Alcohol, Aloe Barbadensis Leaf Extract, Chamomilla Recutita Flower Extract, Citric Acid, Fragrance, Iodopropynyl Butylcarbamate, Lauryl Glucoside, Phenoxyethanol, Propylene Glycol, Tetrasodium EDTA, Water.